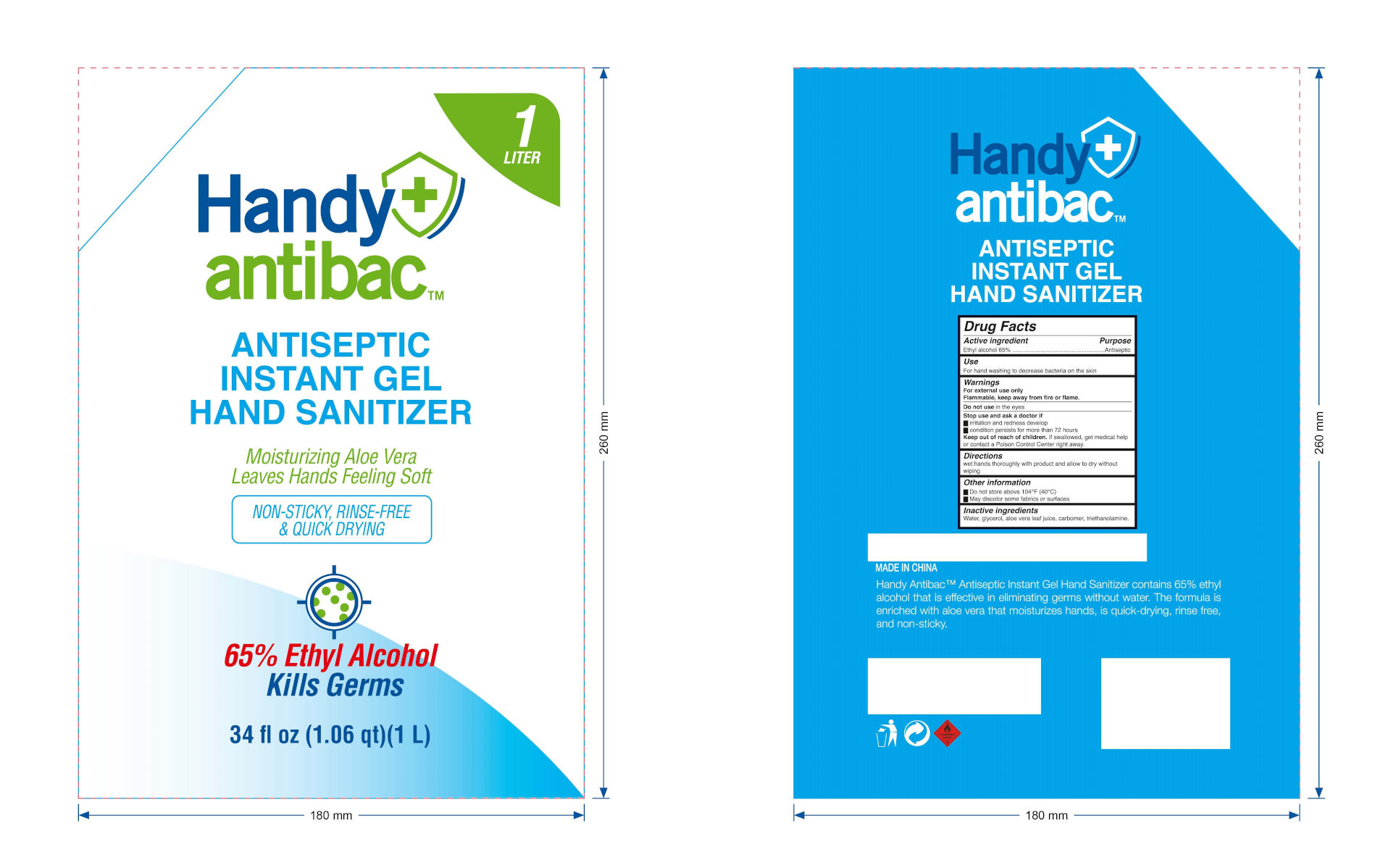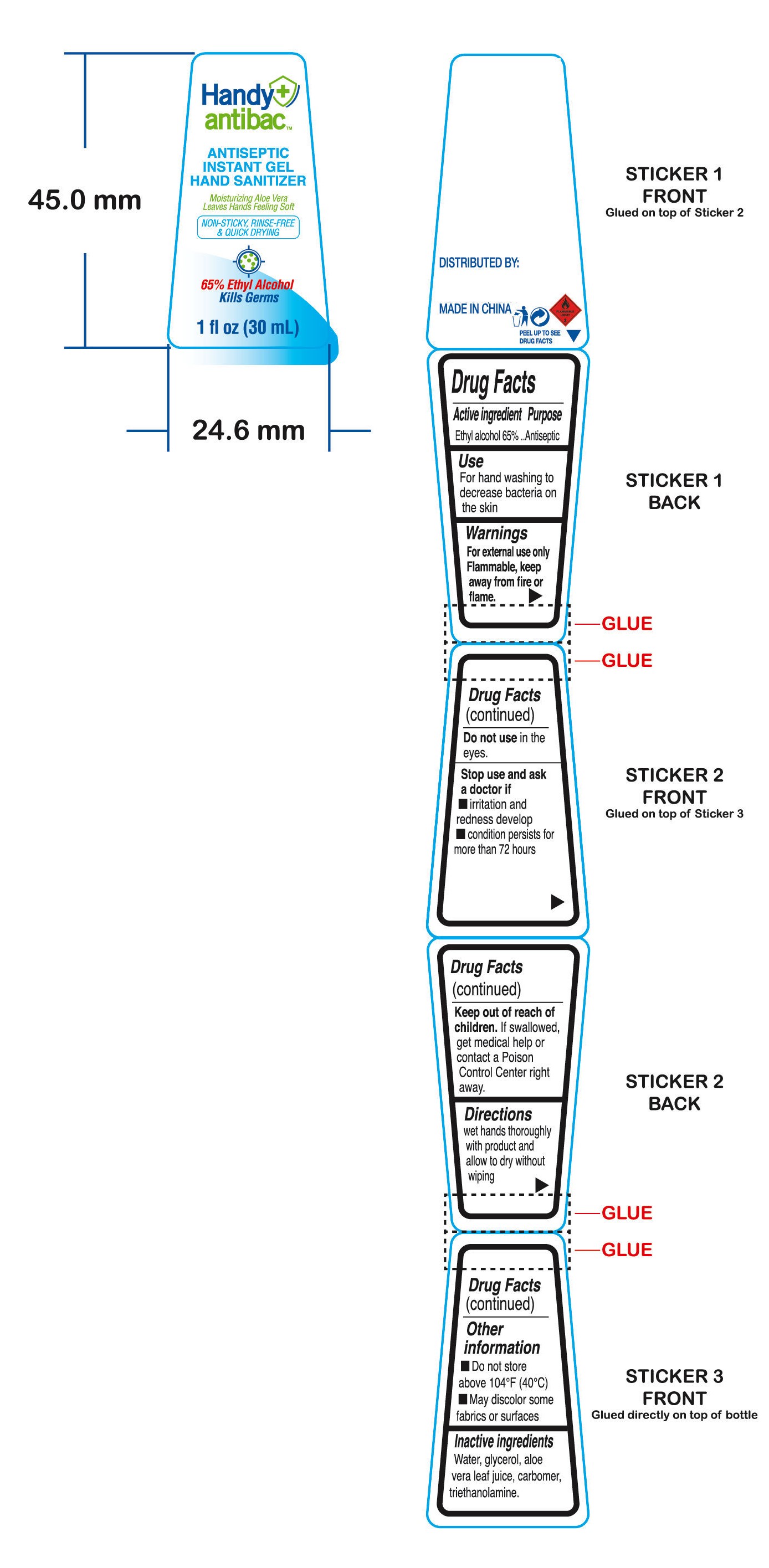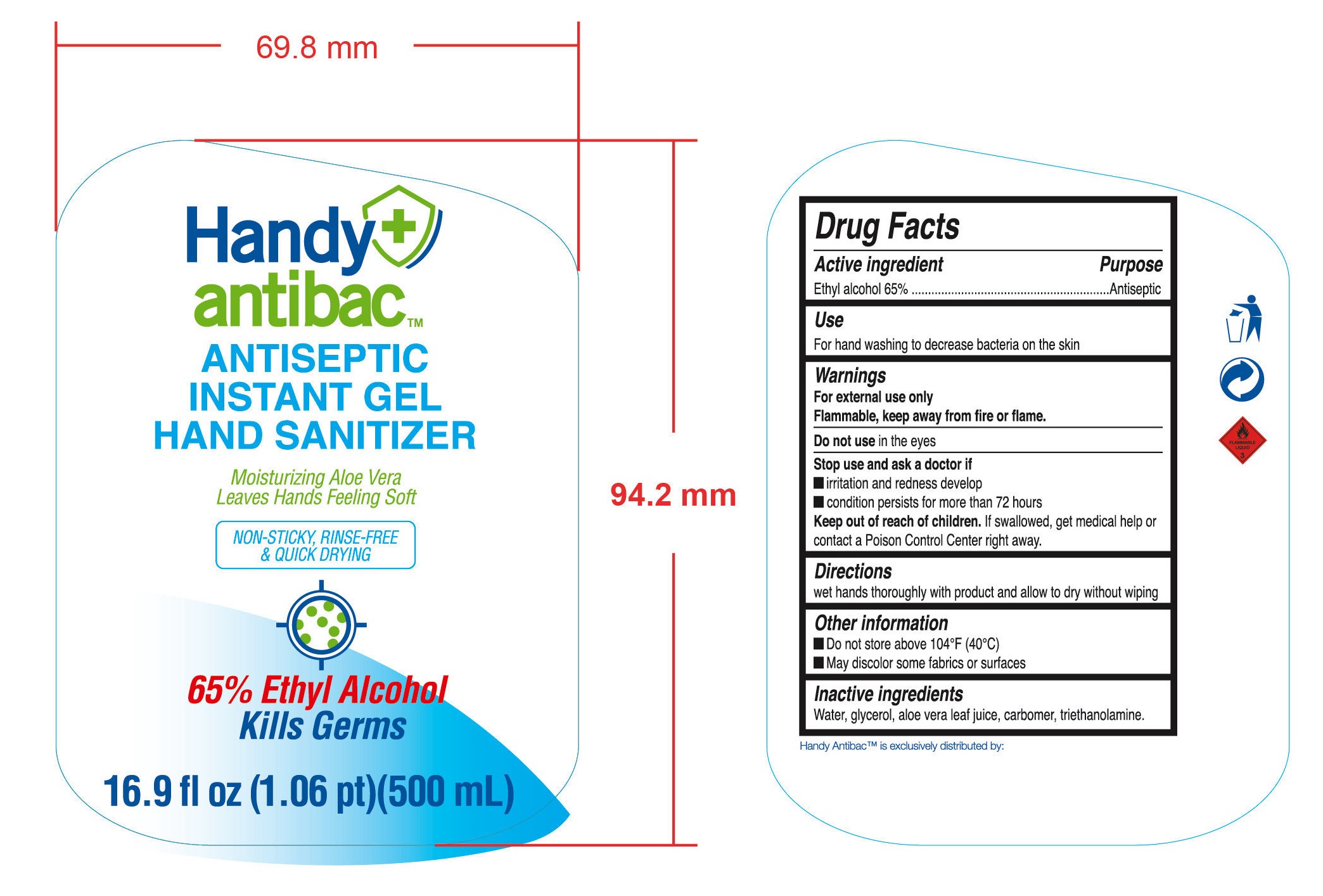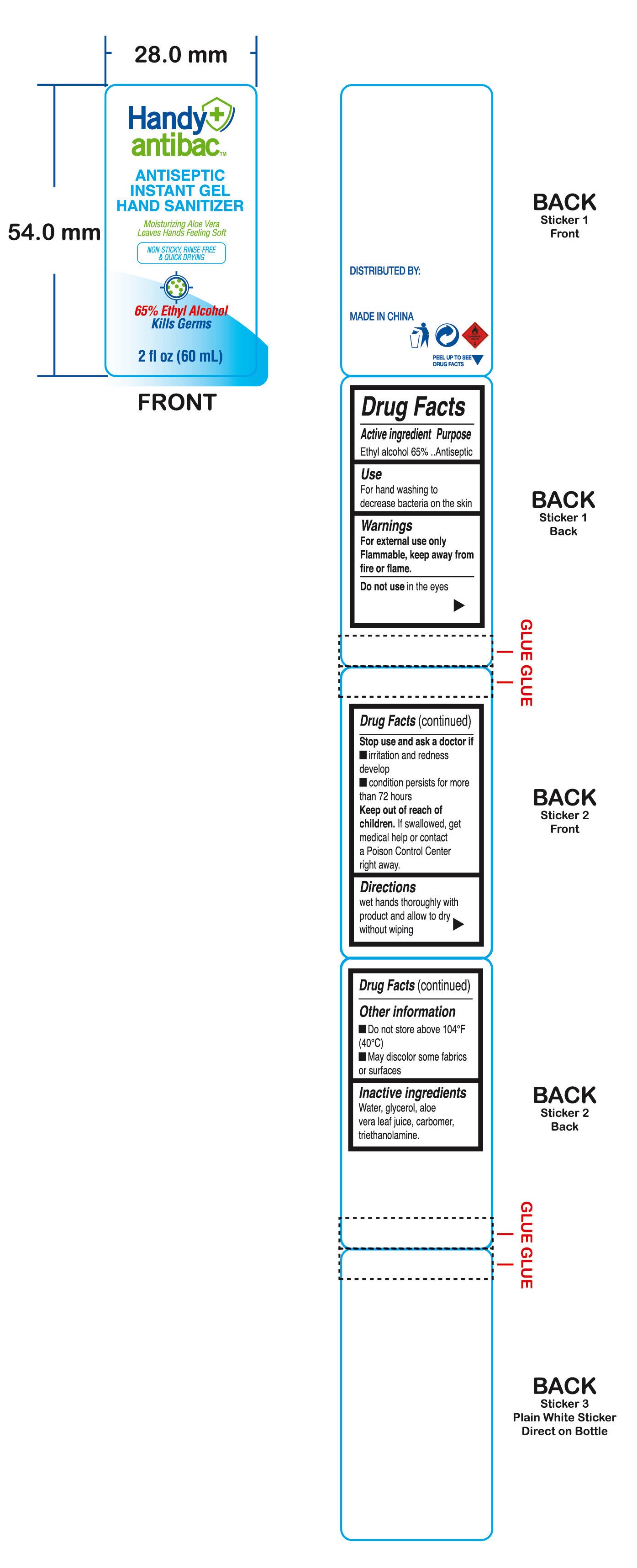 DRUG LABEL: HAND SANITIZER
NDC: 47993-279 | Form: GEL
Manufacturer: NINGBO JIANGBEI OCEAN STAR TRADING CO.,LTD
Category: otc | Type: HUMAN OTC DRUG LABEL
Date: 20201105

ACTIVE INGREDIENTS: ALCOHOL 65 g/112 mL
INACTIVE INGREDIENTS: CARBOMER 940; TRIETHANOLAMINE BENZOATE; ALOE VERA LEAF; WATER; GLYCERIN

47993-279

Active ingredients

Ethyl alcohol 65%

PURPOSE

Antiseptic

Uses：

For hand washing to decrease bacteria on th skin.

Warnings:

For external use only.

Flammable，Keep away from heat or flame.

Do not use in the eyes

Stop use and ask a doctor if

- irritation and redness develop.
- condition persists for more than 72 hours.

Keep out of reach of children. If swallowed, get medical help or contact a Poison Control Center right away.

Directions:

Wet hands thoroughly with product and allow to dry without wiping.

Other information

- Do not store above 104℉(40℃)
- May discolor some fabrics or surfaces

Inactive Ingredients:

Water,glycerol,aloe vera leaf juice,carbomer,triethanolamine.